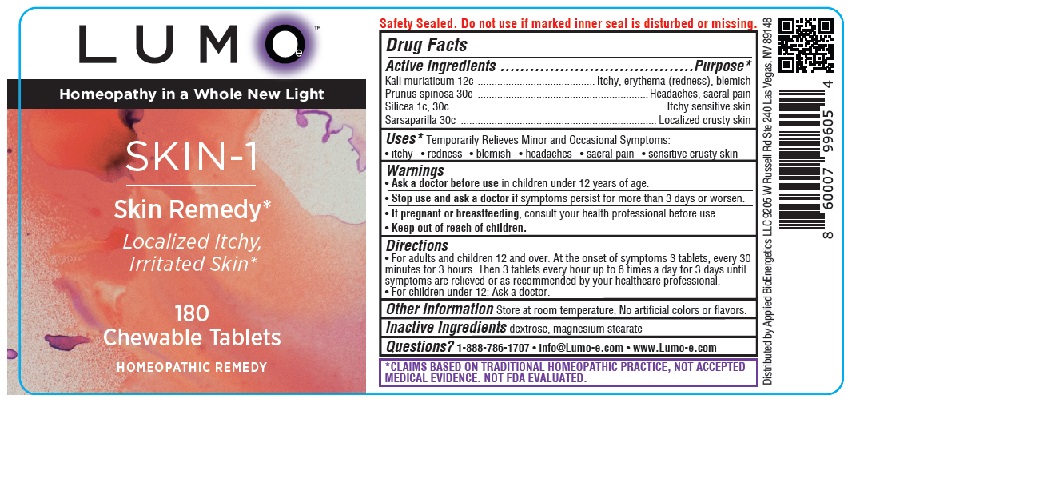 DRUG LABEL: LUMOe SKIN1 Skin Remedy
NDC: 81425-007 | Form: TABLET, CHEWABLE
Manufacturer: Applied Bioenergetics, LLC
Category: homeopathic | Type: HUMAN OTC DRUG LABEL
Date: 20251110

ACTIVE INGREDIENTS: POTASSIUM CHLORIDE 12 [hp_C]/1 1; PRUNUS SPINOSA FLOWER BUD 30 [hp_C]/1 1; SILICON DIOXIDE 30 [hp_C]/1 1; SMILAX ORNATA ROOT 30 [hp_C]/1 1
INACTIVE INGREDIENTS: DEXTROSE; MAGNESIUM STEARATE

LUMOe SKIN-1 Skin Remedy

Drug Facts

Active Ingredients
Kali muriaticum 12c
Prunus spinosa 30c
Silicea 30c
Sarsaparilla 30c

Purpose*
Kali muriaticum .......................................... Itchy, erythema (redness), blemish
Prunus spinosa ............................................................. Headaches, sacral pain
Silicea .................................................................................. Itchy sensitive skin
Sarsaparilla ...................................................................... Localized crusty skin

INDICATIONS AND USAGE

Uses*Temporarily Relieves Minor and Occasional Symptoms:
• itchy • redness • blemish • headaches • sacral pain • sensitive crusty skin

Warnings
• Ask a doctor before use in children under 12 years of age.
• Stop use and ask a doctor if symptoms persist for more than 3 days or worsen.
• If pregnant or breastfeeding, consult your health professional before use.

• Keep out of reach of children.

Directions
• For adults and children 12 and over: At the onset of symptoms 3 tablets, every 30
minutes for 3 hours. Then 3 tablets every hour up to 6 times a day for 3 days until
symptoms are relieved or as recommended by your healthcare professional.
• For children under 12: Ask a doctor.

Other Information Store at room temperature. No artificial colors or flavors.

Inactive Ingredients dextrose, magnesium stearate

QUESTIONS

Questions? 1-888-786-1707 • info@Lumo-e.com • www.Lumo-e.com

*CLAIMS BASED ON TRADITIONAL HOMEOPATHIC PRACTICE, NOT ACCEPTED
MEDICAL EVIDENCE. NOT FDA EVALUATED.

LUMOe SKIN-1 Remedy* Localized Itchy, Irritated Skin* Labeling

LUMOe

Homeopathy in a Whole New Light

SKIN-1
Skin Remedy*
Localized Itchy,
Irritated Skin*

180
Chewable Tablets
HOMEOPATHIC REMEDY

Distributed by Applied BioEnergetics LLC 9205 W Russell Rd Ste 240 Las Vegas, NV 89148

res